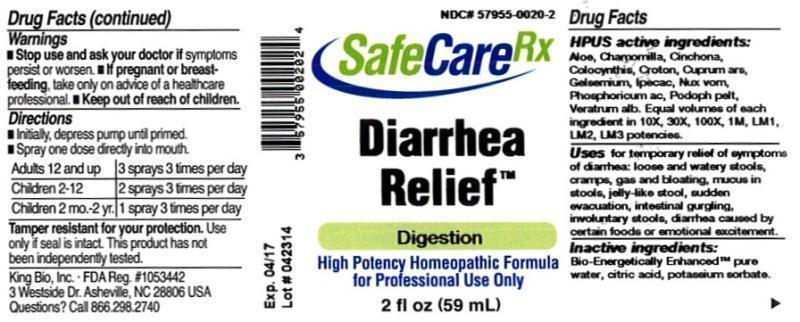 DRUG LABEL: Diarrhea Relief
NDC: 57955-0020 | Form: LIQUID
Manufacturer: King Bio Inc.
Category: homeopathic | Type: HUMAN OTC DRUG LABEL
Date: 20140508

ACTIVE INGREDIENTS: ALOE 10 [hp_X]/59 mL; MATRICARIA RECUTITA 10 [hp_X]/59 mL; CINCHONA OFFICINALIS BARK 10 [hp_X]/59 mL; CITRULLUS COLOCYNTHIS FRUIT PULP 10 [hp_X]/59 mL; CROTON TIGLIUM SEED 10 [hp_X]/59 mL; CUPRIC ARSENITE 10 [hp_X]/59 mL; GELSEMIUM SEMPERVIRENS ROOT 10 [hp_X]/59 mL; IPECAC 10 [hp_X]/59 mL; STRYCHNOS NUX-VOMICA SEED 10 [hp_X]/59 mL; PHOSPHORIC ACID 10 [hp_X]/59 mL; PODOPHYLLUM 10 [hp_X]/59 mL; VERATRUM ALBUM ROOT 10 [hp_X]/59 mL
INACTIVE INGREDIENTS: WATER; CITRIC ACID MONOHYDRATE; POTASSIUM SORBATE

Diarrhea Relief™

ACTIVE INGREDIENT

Drug Facts__________________________________________________________________________________________________________

HPUS activeingredients: Aloe socotrina, Chamomilla, Cinchona officinalis, Colocynthis, Croton tiglium, Cuprum arsenicosum, Gelsemium sempervirens, Ipecacuanha, Nux vomica, Phosphoricum acidum, Podophyllum peltatum, Veratrum album. Equal volumes of each ingredient in 10X, 30X, 100X, 1M, LM1, LM2, LM3 potencies.

INDICATIONS AND USAGE

Uses for temporary relief of symptoms of diarrhea: loose and watery stools, cramps, gas and bloating, mucus in stools, jelly-like stool, sudden evacuation, intestinal gurgling, involuntary stools, diarrhea caused by certain foods or emotional excitement.

Inactive Ingredients:

Bio-Energetically Enhanced™ pure water, citric acid and potassium sorbate.

Warnings

- Stop use and ask your doctor if symptoms persist or worsen.
- If pregnant or breast-feeding, take only on advice of a healthcare professional.

- Keep out of reach of children.

Directions

- Initially, depress pump until primed.
- Spray one dose directly into mouth.
- Adults 12 and up: 3 sprays 3 times per day.
- Children 2-12: 2 sprays 3 times per day.
- Children 2 mo-yr: 1 spray 3 times per day.

OTHER SAFETY INFORMATION

Tamper resistant for your protection. Use only if safety seal is intact. This product has not been independently tested.

PURPOSE

Uses for temporary relief of symptoms of diarrhea:

- loose and watery stools
- cramps, gas and bloating
- mucus in stools
- jelly-like stool
- sudden evacuation
- intestinal gurgling
- involuntary stools
- diarrhea caused by certain foods or emotional excitement